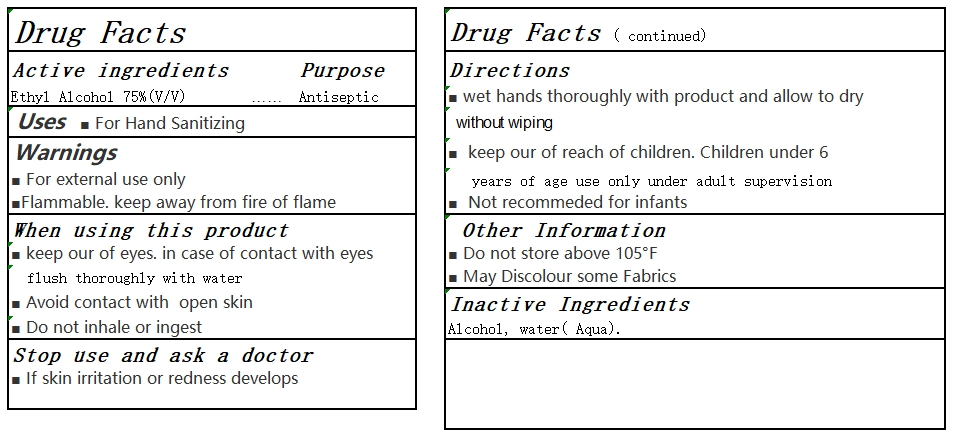 DRUG LABEL: Alcohol wet wipes
NDC: 76896-001 | Form: CLOTH
Manufacturer: Zhejiang Bing'er Non Woven Fabric Co.,Ltd.
Category: otc | Type: HUMAN OTC DRUG LABEL
Date: 20220115

ACTIVE INGREDIENTS: ALCOHOL 75 g/100 g
INACTIVE INGREDIENTS: WATER

76896-001 Alcohol wet wipes

Active Ingredient

Ethyl Alcohol 75%(V/V)

Purpose

Antiseptic

USE

For Hand Sanitizing

Warning

For external use only
Flammable. keep away from fire of flame

When using this product
■ keep our of eyes. in case of contact with eyes
flush thoroughly with water
■ Avoid contact with open skin
■ Do not inhale or ingest
Stop use and ask a doctor
■ If skin irritation or redness develops

KEEP OUT OF REACH OF CHILDREN

■ keep our of reach of children. Children under 6
years of age use only under adult supervision

Directions

■ wet hands thoroughly with product and allow to dry
without wiping

Inactive ingredients

Alcohol, water(Aqua).